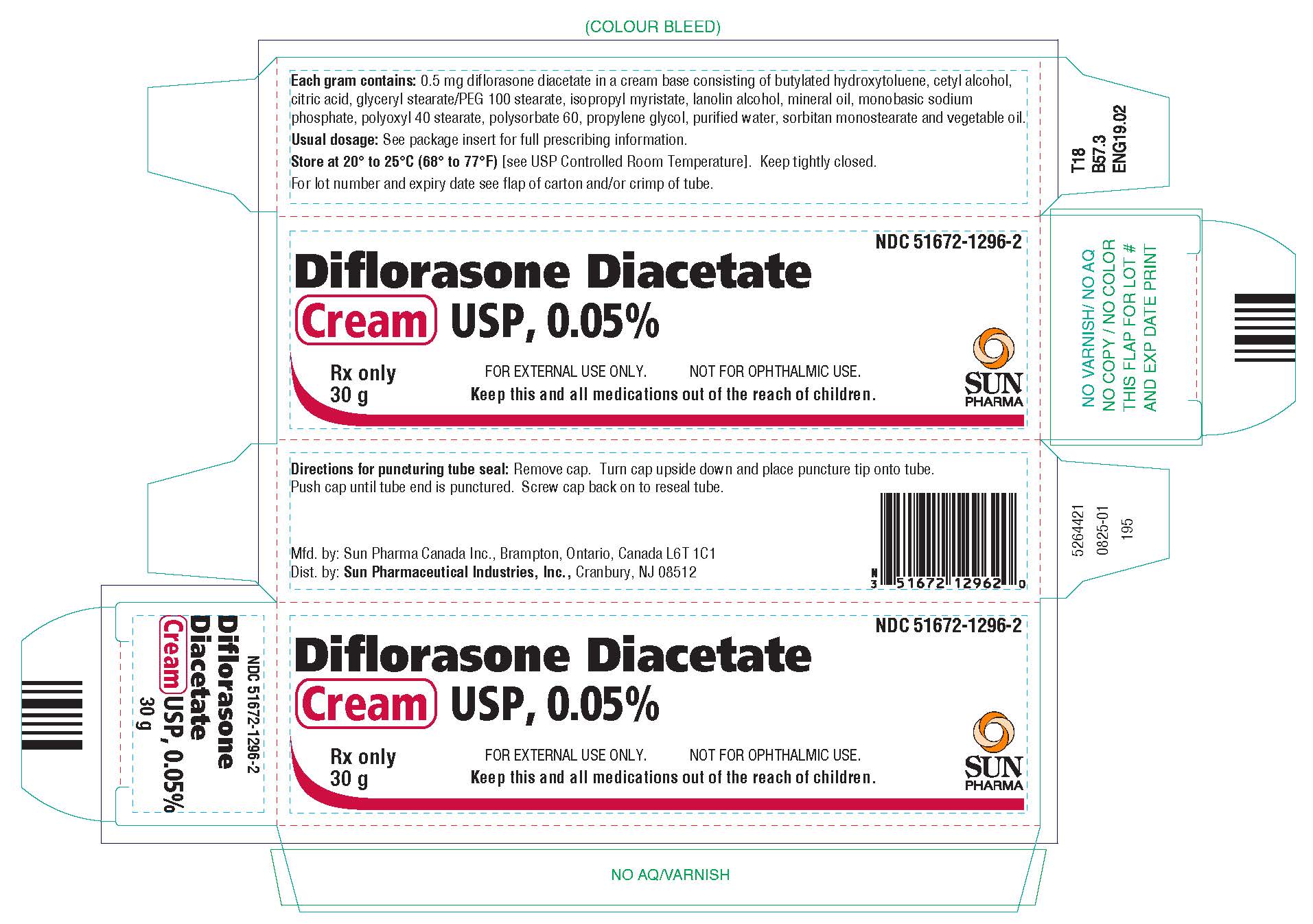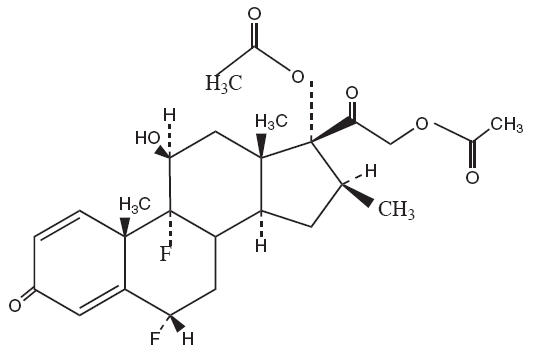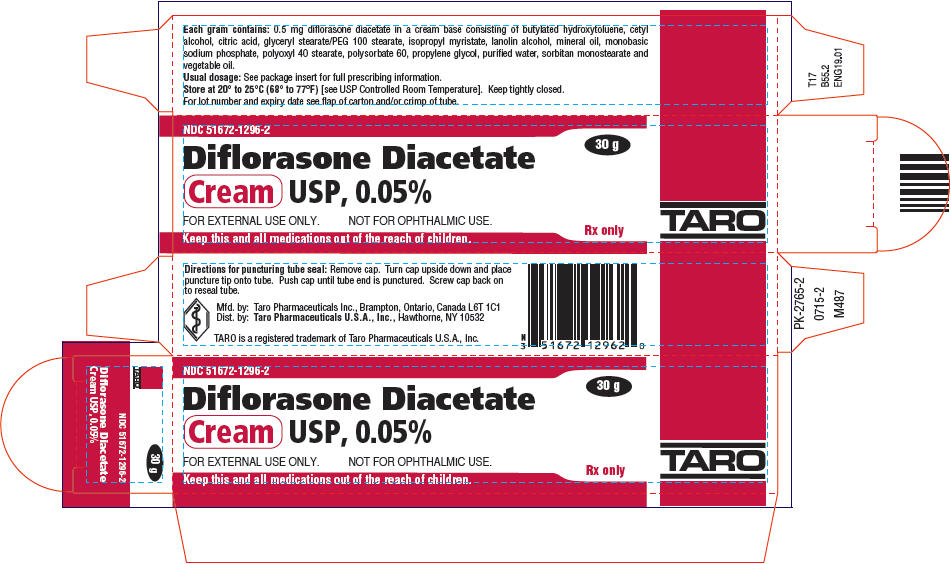 DRUG LABEL: Diflorasone Diacetate
NDC: 51672-1296 | Form: CREAM
Manufacturer: Sun Pharmaceutical Industries, Inc.
Category: prescription | Type: HUMAN PRESCRIPTION DRUG LABEL
Date: 20250922

ACTIVE INGREDIENTS: DIFLORASONE DIACETATE 0.5 mg/1 g
INACTIVE INGREDIENTS: WATER; CITRIC ACID MONOHYDRATE; GLYCERYL MONOSTEARATE; MINERAL OIL; LANOLIN ALCOHOLS; ISOPROPYL MYRISTATE; CETYL ALCOHOL; POLYSORBATE 60; SORBITAN MONOSTEARATE; PALM OIL; SOYBEAN OIL; PEG-100 STEARATE; POLYOXYL 40 STEARATE; BUTYLATED HYDROXYTOLUENE; PROPYLENE GLYCOL; SODIUM PHOSPHATE, MONOBASIC, UNSPECIFIED FORM

Diflorasone Diacetate
Cream USP, 0.05%

Rx only

For External Use Only - Not for Ophthalmic Use.

DESCRIPTION

Diflorasone diacetate cream USP, 0.05% contains the active compound diflorasone diacetate, a synthetic corticosteroid for topical dermatological use.

Chemically, diflorasone diacetate is 6α, 9α-difluoro-11β,17,21-trihydroxy-16-methylpregna-1,4-diene-3,20-dione 17,21 diacetate, with the empirical formula C26H32F2O7, a molecular weight of 494.5, and the following structural formula:

Each gram of diflorasone diacetate cream USP, 0.05% contains 0.5 mg diflorasone diacetate in a cream base consisting of butylated hydroxytoluene, cetyl alcohol, citric acid, glyceryl stearate/PEG 100 stearate, isopropyl myristate, lanolin alcohol, mineral oil, monobasic sodium phosphate, polyoxyl 40 stearate, polysorbate 60, propylene glycol, purified water, sorbitan monostearate and vegetable oil.

CLINICAL PHARMACOLOGY

Like other topical corticosteroids, diflorasone diacetate has anti-inflammatory, anti-pruritic, and vasoconstrictive actions. The mechanism of the anti-inflammatory activity of the topical corticosteroids, in general, is unclear. However, corticosteroids are thought to act by the induction of phospholipase A2inhibitory proteins collectively called lipocortins. It is postulated that these proteins control the biosynthesis of potent mediators of inflammation such as prostaglandins and leukotrienes by inhibiting the release of their common precursor, arachidonic acid. Arachidonic acid is released from membrane phospholipids by phospholipase A2.

Pharmacokinetics

The extent of percutaneous absorption of topical corticosteroids is determined by many factors including the vehicle and the integrity of the epidermal barrier. Occlusive dressings with hydrocortisone for up to 24 hours have not been demonstrated to increase penetration; however, occlusion of hydrocortisone for 96 hours markedly enhances penetration. Topical corticosteroids can be absorbed from normal intact skin. Inflammation and/or other disease processes in the skin may increase percutaneous absorption. Studies performed with diflorasone diacetate cream indicate that it is in the high range of potency as compared with other topical corticosteroids.

INDICATION AND USAGE

Diflorasone diacetate cream USP, 0.05% is a high potency corticosteroid indicated for the relief of the inflammatory and pruritic manifestations of corticosteroid-responsive dermatoses.

CONTRAINDICATIONS

Diflorasone diacetate cream USP is contraindicated in those patients with a history of hypersensitivity to any of the components of the preparation.

PRECAUTIONS

General

Systemic absorption of topical corticosteroids can produce reversible hypothalamic-pituitary-adrenal (HPA) axis suppression with the potential for glucocorticosteroid insufficiency after withdrawal of treatment. Manifestations of Cushing's syndrome, hyperglycemia, and glucosuria can also be produced in some patients by systemic absorption of topical corticosteroids while on treatment.

Patients receiving a large dose of a higher potency topical steroid applied to a large surface area or under an occlusive dressing should be evaluated periodically for evidence of HPA axis suppression. This may be done by using the ACTH-stimulation, A.M. plasma cortisol, and urinary free-cortisol tests.

This product has a greater ability to produce adrenal suppression than does diflorasone diacetate ointment USP, 0.05%. At 30 g per day (applied as 15 g twice daily) diflorasone diacetate cream USP, 0.05% was shown to cause inhibition of the HPA axis in one of two patients following application for one week to psoriatic skin. At 15 g per day (applied as 7.5 g twice daily) diflorasone diacetate cream USP, 0.05% was shown to cause mild inhibition of the HPA axis in one of five patients following application for one week to diseased skin (psoriasis or atopic dermatitis). These effects were reversible upon discontinuation of treatment. By comparison, diflorasone diacetate ointment USP, 0.05% did not produce significant HPA axis suppression when used in divided doses at 30 g per day for one week in patients with psoriasis or atopic dermatitis.

If HPA axis suppression is noted, an attempt should be made to withdraw the drug, to reduce the frequency of application, or to substitute a less potent corticosteroid. Recovery of HPA axis function is generally prompt and complete upon discontinuation of topical corticosteroids. Infrequently, signs and symptoms of glucocorticosteroid insufficiency may occur, requiring supplemental systemic corticosteroids. For information on systemic supplementation, see prescribing information for those products.

Pediatric patients may be more susceptible to systemic toxicity from equivalent doses due to their larger skin surface to body mass ratios (see PRECAUTIONS: Pediatric Use).

If irritation develops, diflorasone diacetate cream USP should be discontinued and appropriate therapy instituted. Allergic contact dermatitis with corticosteroids is usually diagnosed by observing failure to heal rather than noting a clinical exacerbation as with most topical products not containing corticosteroids. Such an observation should be corroborated with appropriate diagnostic patch testing.

If concomitant skin infections are present or develop, an appropriate antifungal or antibacterial agent should be used. If a favorable response does not occur promptly, use of diflorasone diacetate cream USP should be discontinued until the infection has been adequately controlled.

Diflorasone diacetate cream USP, 0.05% should not be used in the treatment of rosacea or perioral dermatitis, and it should not be used on the face, groin, or axillae.

Information for Patients

Patients using topical corticosteroids should receive the following information and instructions:

1. The medication is to be used as directed by the physician. It is for external use only. Avoid contact with the eyes.
2. The medication should not be used for any disorder other than that for which it was prescribed.
3. The treated skin area should not be bandaged or otherwise covered or wrapped so as to be occlusive unless directed by the physician.
4. Patients should report to their physician any signs of local adverse reactions.

Laboratory Tests

The following tests may be helpful in evaluating patients for HPA axis suppression:

- ACTH-stimulation test
- A.M. plasma-cortisol test
- Urinary free-cortisol test

Carcinogenesis, Mutagenesis, Impairment of Fertility

Long-term animal studies have not been performed to evaluate the carcinogenic potential of diflorasone diacetate.

Diflorasone diacetate was not found to be mutagenic in a micronucleus test in rats at dosages of 2400 mg/kg.

Studies in the rat following topical administration at doses up to 0.5 mg/kg revealed no effects on fertility.

Pregnancy

Teratogenic effects

Pregnancy Category C

Corticosteroids have been shown to be teratogenic in laboratory animals when administered systemically at relatively low dosage levels. Some corticosteroids have been shown to be teratogenic after dermal application to laboratory animals.

Diflorasone diacetate has been shown to be teratogenic (cleft palate) in rats when applied topically at a dose of approximately 0.001 mg/kg/day to the shaven thorax of pregnant animals. This is approximately 0.3 times the human topical dose of diflorasone diacetate cream USP, 0.05%. When pregnant rats were treated topically with approximately 0.5 mg/kg/day, uterine deaths were higher in the treated animals than in control animals.

In rabbits, cleft palate was seen when diflorasone diacetate was applied in topical doses as low as 20 mg/kg/day. In addition, fetal weight was depressed and litter sizes were smaller.

There are no adequate and well-controlled studies of the teratogenic potential of diflorasone diacetate in pregnant women. Diflorasone diacetate cream USP should be used during pregnancy only if the potential benefit justifies the potential risk to the fetus.

Nursing Mothers

Systemically administered corticosteroids appear in human milk and could suppress growth, interfere with endogenous corticosteroid production, or cause other untoward effects. It is not known whether topical administration of corticosteroids could result in sufficient systemic absorption to produce detectable quantities in human milk. Because many drugs are excreted in human milk, caution should be exercised when diflorasone diacetate cream USP is administered to a nursing woman.

Pediatric Use

Safety and effectiveness of diflorasone diacetate cream USP, 0.05% in pediatric patients have not been established. Because of a higher ratio of skin surface area to body mass, pediatric patients are at a greater risk than adults of HPA-axis suppression when they are treated with topical corticosteroids. They are, therefore, also at greater risk of glucocorticosteroid insufficiency after withdrawal of treatment and of Cushing's syndrome while on treatment. Adverse effects including striae have been reported with inappropriate use of topical corticosteroids in pediatric patients.

HPA axis suppression, Cushing's syndrome, and intracranial hypertension have been reported in pediatric patients receiving topical corticosteroids. Manifestations of adrenal suppression in pediatric patients include linear growth retardation, delayed weight gain, low plasma cortisol levels, and absence of response to ACTH stimulation. Manifestations of intracranial hypertension include bulging fontanelles, headaches, and bilateral papilledema.

ADVERSE REACTIONS

The following local adverse reactions have been reported infrequently with other topical corticosteroids, and they may occur more frequently with the use of occlusive dressings, especially with higher potency corticosteroids. These reactions are listed in an approximate decreasing order of occurrence: burning, itching, irritation, dryness, folliculitis, acneiform eruptions, hypopigmentation, perioral dermatitis, allergic contact dermatitis, secondary infections, skin atrophy, striae, and miliaria.

To report SUSPECTED ADVERSE REACTIONS, contact Sun Pharmaceutical Industries, Inc. at 1-866-923-4914 or FDA at 1-800-FDA-1088 or www.fda.gov/medwatch.

OVERDOSAGE

Topically applied diflorasone diacetate cream USP, 0.05% can be absorbed in sufficient amounts to produce systemic effects (see PRECAUTIONS).

DOSAGE AND ADMINISTRATION

Diflorasone diacetate cream USP, 0.05% should be applied to the affected area twice daily.

HOW SUPPLIED

Diflorasone diacetate cream USP, 0.05% is available in 15 g (NDC 51672-1296-1), 30 g (NDC 51672-1296-2) and 60 g (NDC 51672-1296-3) tubes.

STORAGE AND HANDLING

Store at 20° to 25° C (68° to 77° F)[see USP Controlled Room Temperature]. Keep tightly closed.

Mfd. by: Sun Pharma Canada Inc., Brampton, Ontario, Canada L6T 1C1

Dist. by: Sun Pharmaceutical Industries, Inc., Cranbury, NJ 08512

Revised: September 2025

5264420-0925-01 358

PRINCIPAL DISPLAY PANEL - 30 g Tube Carton

NDC 51672-1296-2

30 g

Diflorasone Diacetate
Cream USP, 0.05%

FOR EXTERNAL USE ONLY.
NOT FOR OPHTHALMIC USE.

Rx only

Keep this and all medications out of the reach of children.